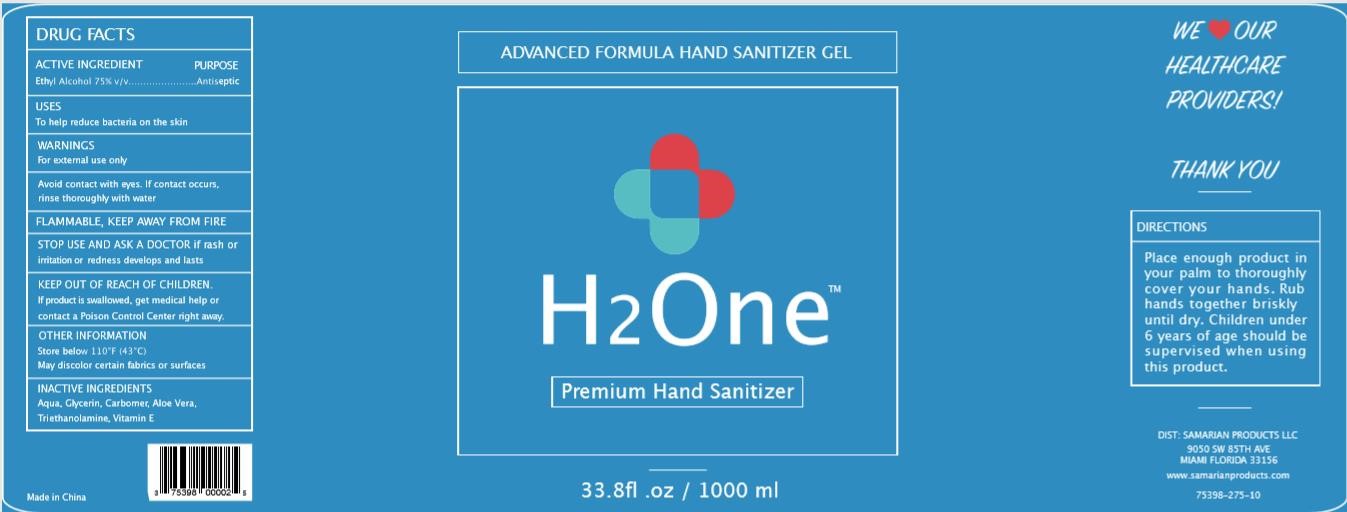 DRUG LABEL: H2One
NDC: 75742-006 | Form: GEL
Manufacturer: Zhejiang Guoyao Jingyue Aerosol Co., Ltd.
Category: otc | Type: HUMAN OTC DRUG LABEL
Date: 20260105

ACTIVE INGREDIENTS: ALCOHOL 75 mL/100 mL
INACTIVE INGREDIENTS: CARBOMER HOMOPOLYMER, UNSPECIFIED TYPE; ALOE VERA LEAF; TROLAMINE; .ALPHA.-TOCOPHEROL; GLYCERIN; WATER

Active Ingredient

Ethyl Alcohol 75%

Purpose

Antiseptic

Uses

To help reduce bacteria on the skin

Warnings

For external use only

Avoid contact with eyes. If contact occurs, rinse thoroughly with water.

FLAMMABLE, KEEP AWAY FROM FIRE

Stop use and ask a doctor if rash or irritation or redness develops and lasts.

Keep out of reach of children

If product is swallowed, get medical help or contact a Poison Control Center right away.

Directions

Place enough product in your palm to thoroughly cover your hands. Rub hands together briskly until dry. Children under 6 years of age should be supervised when using this product.

Other information

Store below 110F(43C)

May discolor certain fabrics or surfaces

Inactive Ingredients

Aqua

Glycerin

Carbomer

Aloe Vera

Triethanolamine

Vitamin E